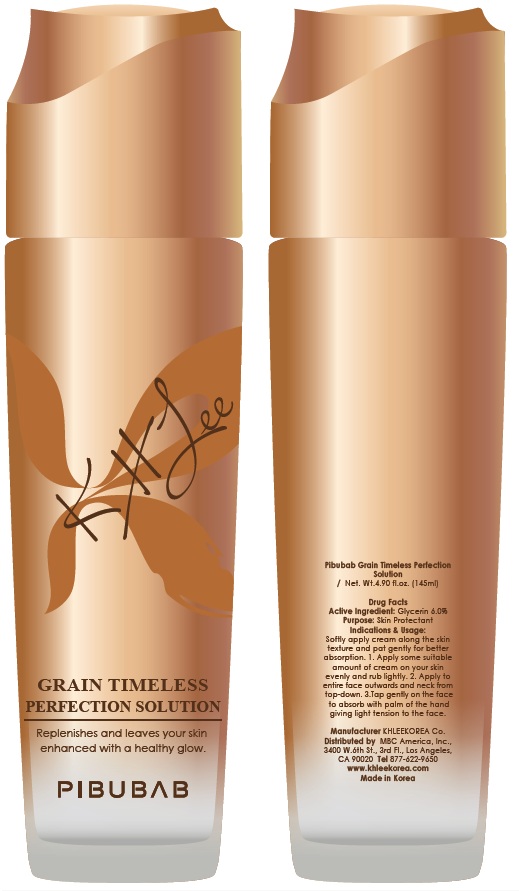 DRUG LABEL: Grain Timeless Perfection
NDC: 70567-080 | Form: SOLUTION
Manufacturer: KHLEEKOREA
Category: otc | Type: HUMAN OTC DRUG LABEL
Date: 20160418

ACTIVE INGREDIENTS: Glycerin 8.7 g/145 mL
INACTIVE INGREDIENTS: Water; Butylene Glycol

ACTIVE INGREDIENT

Active Ingredient: Glycerin 6.0%

INACTIVE INGREDIENT

Inactive Ingredients: Water, Butylene Glycol, Sodium Hyaluronate, PPG-26-Buteth-26 /PEG-40 Hydrogenated Castor Oil Carbomer, 1,2-Hexanediol, Honey Extract, Wild Ginseng Root Culture Extract, Chrysanthemum Morifolium Flower Extract, Citrus Unshiu Fruit Extract, Oenothera Biennis (Evening Primrose) Oil, Phellodendron Amurense Bark Extract, Coptis Chinensis Root Extract, Scutellaria Baicalensis Root Extract, Rhus Semialata Gall Extract, Silkworm Extract, Oryza Sativa (Rice) Extract, Sesamum Indicum (Sesame) Seed Extract, Perilla Ocymoides Seed Extract, Phaseolus Radiatus Seed Extract, Triticum Turgidum Durum (Wheat) Seed Extract, Phaseolus Angularis Seed Extract, Glycine Max (Soybean) Seed Extract, Pinus Koraiensis Seed Extract, Glycine Max (Soybean) Seed Extract, Juglans Regia (Walnut) Seed Extract, Arachis Hypogaea (Peanut) Fruit Extract, Prunus Amygdalus Dulcis (Sweet Almond) Seed Extract, Sesamum Indicum (Sesame) Seed Extract, Polygonum Fagopyrum (Buckwheat) Seed Extract, Coix Lacryma-Jobi Ma-yuen Seed Extract, Hordeum Distichon (Barley) Extract, Helianthus Annuus (Sunflower) Seed Extract, Avena Sativa (Oat) Meal Extract, Rosa Canina Seed Extract, Ginkgo Biloba Nut Extract, Phenoxyethanol, Fragrance, Triethanolamine

PURPOSE

Purpose: Skin protectant

It is a skincare solution of skin lotion typed, containg the ingredient extracted from main 20 grains, wild Ginseng root, phellodendron, coptis and scutellaria, soothes skin tired from stress and keeps healthy skin.

WARNINGS

Warnings: 1. If the following symptoms arise upon use of the cosmetic product, immediately discontinue use and consult a dermatologist, for continued use may aggravate the symptoms. A. Redness, swelling, itchiness, stimulation, or other symptoms B. Occurrence of the above symptoms upon exposure to direct sunlight. 2. Do not use on areas with wounds, eczema, or dermatitis. 3. Do not store in areas with extreme heat or cold, or under direct sunlight. 4. Avoid the eye area 5. Keep out of reach of children

KEEP OUT OF REACH OF CHILDREN

INDICATIONS & USAGE

Indications & Usage: Softly apply cream along the skin texture and pat gently for better absorption. 1. Apply some suitable amount of cream on your skin evenly and rub lightly. 2. Apply to entire face outwards and neck from top-down. 3. Tap gently on the face to absorb with palm of the hand giving light tension to the face.

DOSAGE & ADMINISTRATION

Dosage & Administration: Take an adequate amount of this product.